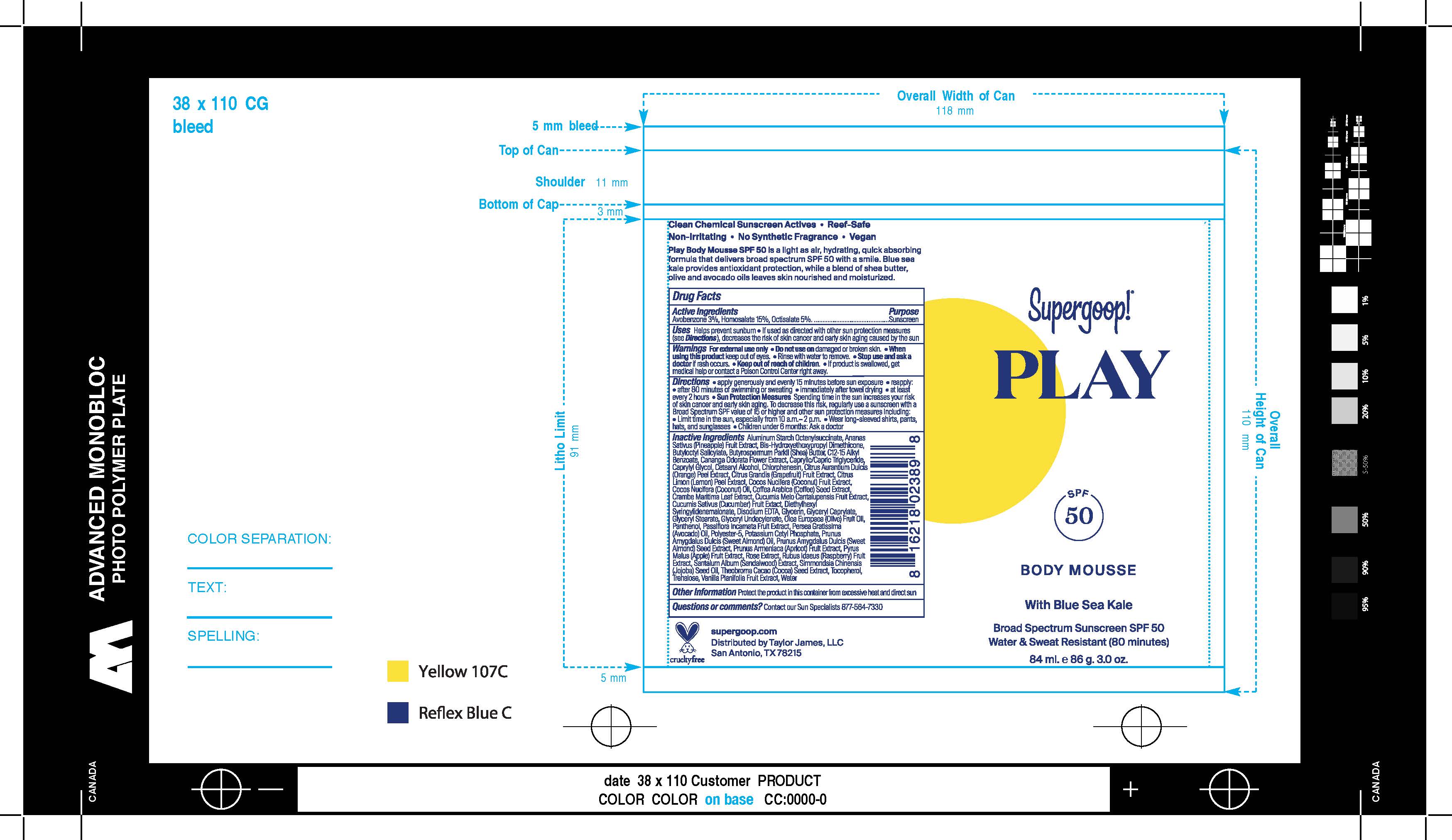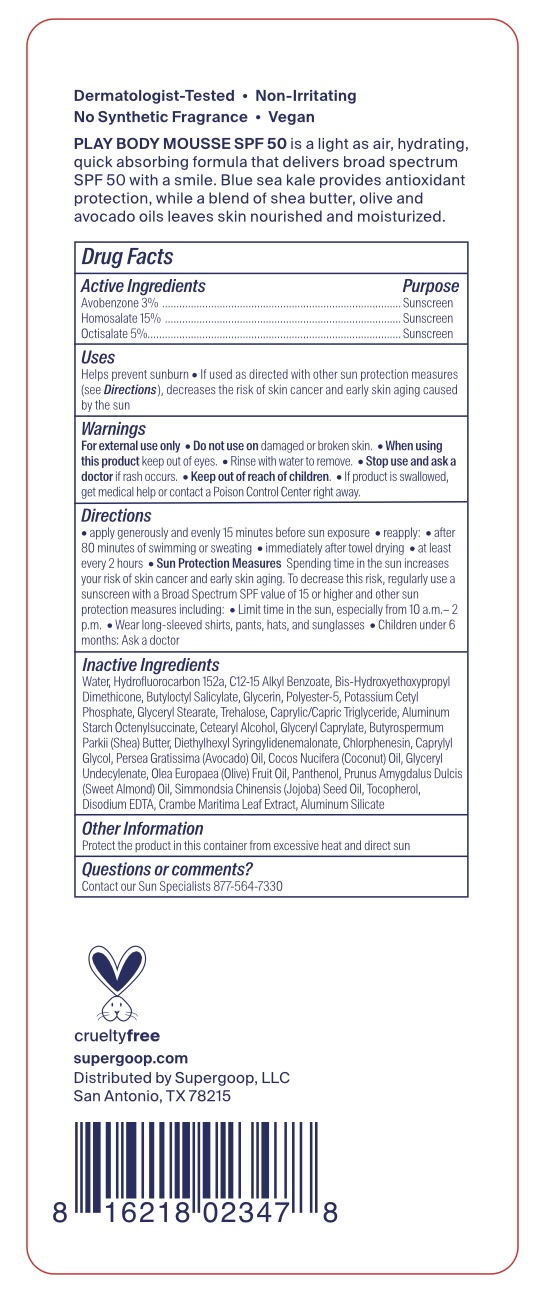 DRUG LABEL: PLAY Body Mousse SPF 50 with Blue Sea Kale
NDC: 75936-656 | Form: LOTION
Manufacturer: Supergoop, LLC
Category: otc | Type: HUMAN OTC DRUG LABEL
Date: 20250813

ACTIVE INGREDIENTS: AVOBENZONE 3 g/100 mL; HOMOSALATE 15 g/100 mL; OCTISALATE 5 g/100 mL
INACTIVE INGREDIENTS: 1,1-DIFLUOROETHANE; ALUMINUM SILICATE; TOCOPHEROL; WATER; POLYESTER-5 (TG-48); POTASSIUM CETYL PHOSPHATE; PUMMELO; SHEA BUTTER; CAPRYLYL GLYCOL; ALKYL (C12-15) BENZOATE; BUTYLOCTYL SALICYLATE; MEDIUM-CHAIN TRIGLYCERIDES; CHLORPHENESIN; GLYCERIN; ALUMINUM STARCH OCTENYLSUCCINATE; PANTHENOL; JOJOBA OIL; CETOSTEARYL ALCOHOL; COCONUT OIL; CRAMBE MARITIMA LEAF; DIETHYLHEXYL SYRINGYLIDENEMALONATE; GLYCERYL MONOSTEARATE; ALMOND OIL; BIS-HYDROXYETHOXYPROPYL DIMETHICONE (37 CST); AVOCADO OIL; EDETATE DISODIUM; GLYCERYL MONOCAPRYLATE; GLYCERYL 1-UNDECYLENATE; OLIVE OIL; TREHALOSE

PLAY Body Mousse SPF 50 with Blue Sea Kale

Active Ingredients Purpose

Avobenzone3% Sunscreen

Homosalate 15% Sunscreen

Octisalate 5% Sunscreen

Uses

Helps Prevent Sunburn
If used as directed with other sun protection measures (see Directions), decreases the risk of skin cancer and early skin aging caused by the sun.

Keep out of reach of children

If product is swallowed, get medical help or contact a poison Control Center right away

WARNINGS

For external use only

Do not use on damaged or broken skin

When using this product keep out of eyes. Rinse with water to remove

Stop use and ask a doctor if rash occurs

Directions

• Apply generously and evenly as the last step in your skincare routine, before makeup and 15 minutes before sun exposure. • Reapply: • after 80 minutes of swimming or sweating. • immediately after towel drying • at least every 2 hours. • Sun Protection Measures. Spending time in the sun increases your risk of skin cancer and early skin aging. To decrease this risk, regularly use a sunscreen with a Broad Spectrum SPF value of 15 or higher and other sun protection measures including: • Limit time in the sun, especially from 10 a.m.-2 p.m. • wear long-sleeved shirts, pants, hats, and sunglasses. • Children under 6 months: ask a doctor.

Inactive Ingredients

Water, Hydrofluorocarbon 152a, C12-15 Alkyl Benzoate, Bis-Hydroxyethoxypropyl Dimethicone, Butyloctyl Salicylate, Glycerin, Polyester-5, Potassium Cetyl Phosphate, Glyceryl Stearate, Trehalose, Caprylic/Capric Triglyceride, Aluminum Starch Octenylsuccinate, Cetearyl Alcohol, Glyceryl Caprylate, Butyrospermum Parkii (Shea) Butter, Diethylhexyl Syringylidenemalonate, Chlorphenesin, Caprylyl Glycol, Persea Gratissima (Avocado) Oil, Cocos Nucifera (Coconut) Oil, Glyceryl Undecylenate, Olea Europaea (Olive) Fruit Oil, Panthenol, Prunus Amygdalus Dulcis (Sweet Almond) Oil, Simmondsia Chinensis (Jojoba) Seed Oil, Tocopherol, Disodium EDTA, Crambe Maritima Leaf Extract, Aluminum Silicate

PACKAGE LABEL

Supergoop!

PLAY

SPF 50

Body Mousse With Blue Sea Kale

Broad Spectrum Suncreen SPF 50

Water and Sweat Resistant (80 minutes)